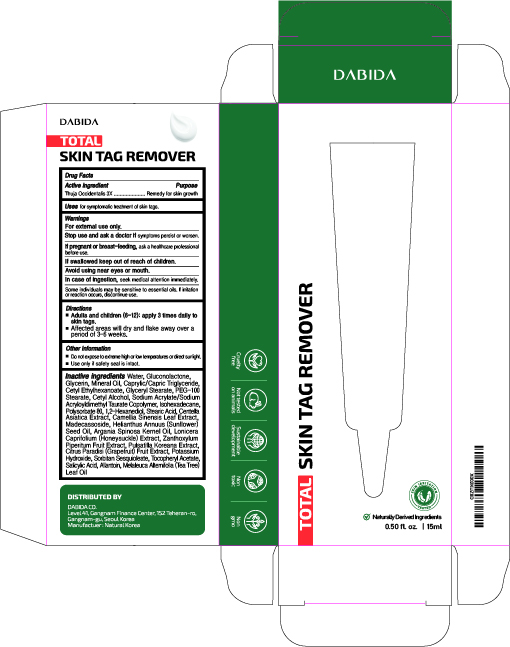 DRUG LABEL: TOTAL SKIN TAG REMOVER
NDC: 74646-0015 | Form: CREAM
Manufacturer: Natural Korea Co., Ltd.
Category: homeopathic | Type: HUMAN OTC DRUG LABEL
Date: 20200811

ACTIVE INGREDIENTS: THUJA OCCIDENTALIS LEAF 3 [hp_X]/15 mL
INACTIVE INGREDIENTS: POLYSORBATE 80; GREEN TEA LEAF; ARGAN OIL; LONICERA CAPRIFOLIUM FLOWER; SORBITAN SESQUIOLEATE; .ALPHA.-TOCOPHEROL ACETATE; SODIUM ACRYLATE/SODIUM ACRYLOYLDIMETHYLTAURATE COPOLYMER (4000000 MW); GLUCONOLACTONE; GLYCERIN; MINERAL OIL; MEDIUM-CHAIN TRIGLYCERIDES; WATER; GLYCERYL MONOSTEARATE; PEG-100 STEARATE; CETYL ALCOHOL; CETYL ETHYLHEXANOATE; ISOHEXADECANE; 1,2-HEXANEDIOL; STEARIC ACID; CENTELLA ASIATICA; MADECASSOSIDE; SUNFLOWER OIL; ZANTHOXYLUM PIPERITUM FRUIT PULP; PULSATILLA KOREANA WHOLE; GRAPEFRUIT; POTASSIUM HYDROXIDE; SALICYLIC ACID; ALLANTOIN; TEA TREE OIL

[OTC-HOMEOPHATIC]
TOTAL SKIN TAG REMOVER : 74646-0015-1